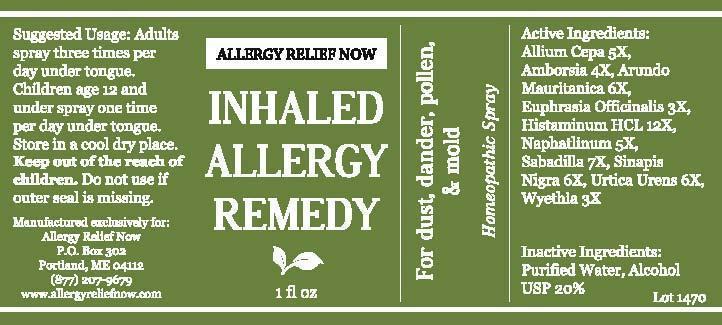 DRUG LABEL: Allergy Relief Now Inhaled Allergy Remedy
NDC: 61727-052 | Form: SPRAY
Manufacturer: Homeocare Laboratories
Category: homeopathic | Type: HUMAN OTC DRUG LABEL
Date: 20140324

ACTIVE INGREDIENTS: ONION 5 [hp_X]/1 [hp_X]; AMBROSIA ARTEMISIIFOLIA 4 [hp_X]/1 [hp_X]; ARUNDO PLINIANA ROOT 6 [hp_X]/1 [hp_X]; EUPHRASIA STRICTA 3 [hp_X]/1 [hp_X]; HISTAMINE 12 [hp_X]/1 [hp_X]; NAPHTHALENE 5 [hp_X]/1 [hp_X]; SCHOENOCAULON OFFICINALE SEED 7 [hp_X]/1 [hp_X]; BLACK MUSTARD SEED 6 [hp_X]/1 [hp_X]; URTICA URENS 6 [hp_X]/1 [hp_X]; WYETHIA HELENIOIDES ROOT 3 [hp_X]/1 [hp_X]
INACTIVE INGREDIENTS: WATER; ALCOHOL

Active Ingredients:

Allium Cepa 5X, Ambrosia 4X, Arundo Mautitanica 6X, Euphrasia Officinalis 3X, Histaminum HCL 12X, Naphatlinum 5X, Sabadilla 7X, Sinapis Nigra 6X, Urtica Urens 6X, Wyethia 3X

Inactive Ingredients:

Purified Water, Alcohol USP 20%

Suggested Usage:

Adults spray three times per day under tongue. Children age 12 and under spray one time per day under tongue. Store in a cool dry place.

INDICATIONS AND USAGE

For dust, dander, pollen, & mold Homeopathic Spray

Keep out of the reach of children

Do not use if outer seal is missing

Allergy Now Inhaled Allergy Remedy 1 fl oz

Concordia_LabelFinal-inhaledallergy-1470.jpg